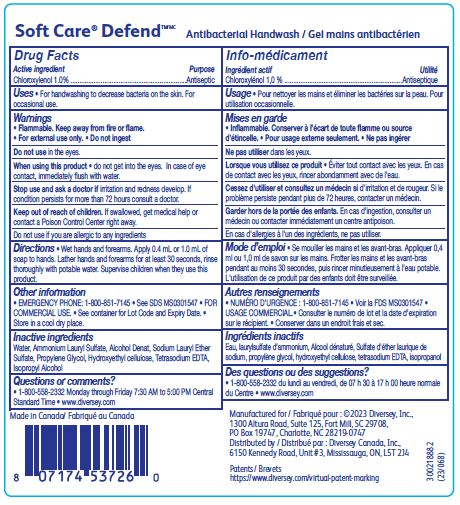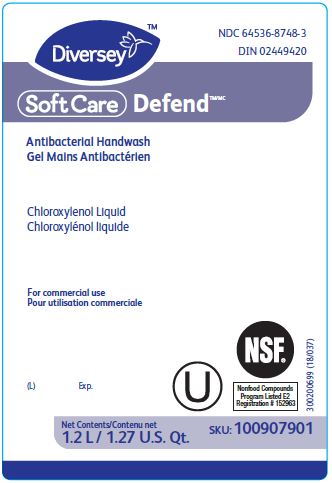 DRUG LABEL: Soft Care Defend Antibacterial Handwash
NDC: 64536-8748 | Form: SOLUTION
Manufacturer: Diversey, Inc.
Category: otc | Type: HUMAN OTC DRUG LABEL
Date: 20251215

ACTIVE INGREDIENTS: CHLOROXYLENOL 1 g/100 mL
INACTIVE INGREDIENTS: WATER; ALCOHOL; PROPYLENE GLYCOL; AMMONIUM LAURYL SULFATE; HYDROXYETHYL CELLULOSE (2000 MPA.S AT 1%); ISOPROPYL ALCOHOL; EDETATE SODIUM; SODIUM LAURETH-3 SULFATE

Drug Facts

Active ingredient

Chloroxylenol 1.0%

Purpose

Antiseptic

Uses

For handwashing to decrease bacteria on the skin.

For occasional use.

Warnings

Flammable. Keep away from fire or flame.

For external use only.

Do not ingest

Do not use in the eyes.

When using this product do not get into the eyes.

In case of eye contact, immediately flush with water.

Stop use and ask a doctor if irritation and redness develop.

If conditions persists for more than 72 hours consult a doctor.

Keep out of reach of children.

If swallowed, get medical help or contact a Poison Control Center right away.

Do not use if you are allergic to any ingredients

Directions

Wet hands and forearms.

Apply 0.4 mL or 1.0 mL of soap to hands.

Lather hands and forearms for at least 30 seconds, rinse thoroughly with potable water.

Supervise children when they use this product.

Other information

EMERGENCY PHONE: 1-800-851-7145

See SDS MS0301547

FOR COMMERCIAL USE.

See container for Lot Code and Expiry Date.

Store in a cool dry place.

Inactive ingredients

Water, Ammonium Lauryl Sulfate, Alcohol Denat, Sodium Lauryl Ether Sulfate, Propylene Glycol, Hydroxyethyl cellulose, Tetrasodium EDTA, Isopropyl Alcohol

Questions or comments?

1-800-558-2332 Monday through Friday 7:30 AM to 5:00 PM Central Standard Time

www.diversey.com

PACKAGE LABEL

NDC 64536-8748-3

DIN 02449420

Diversey

SoftCare Defend

Antibacterial Handwash

Chloroxylenol Liquid

For commercial use

U

NSF

Nonfood Compounds

Program Listed E2

Registration # 152963

(L) Exp.

Net Contents

1.2 L/ 1.27 U.S. Qt.

SKU: 100907901